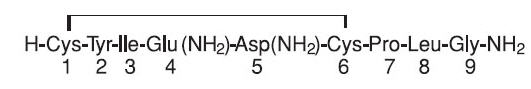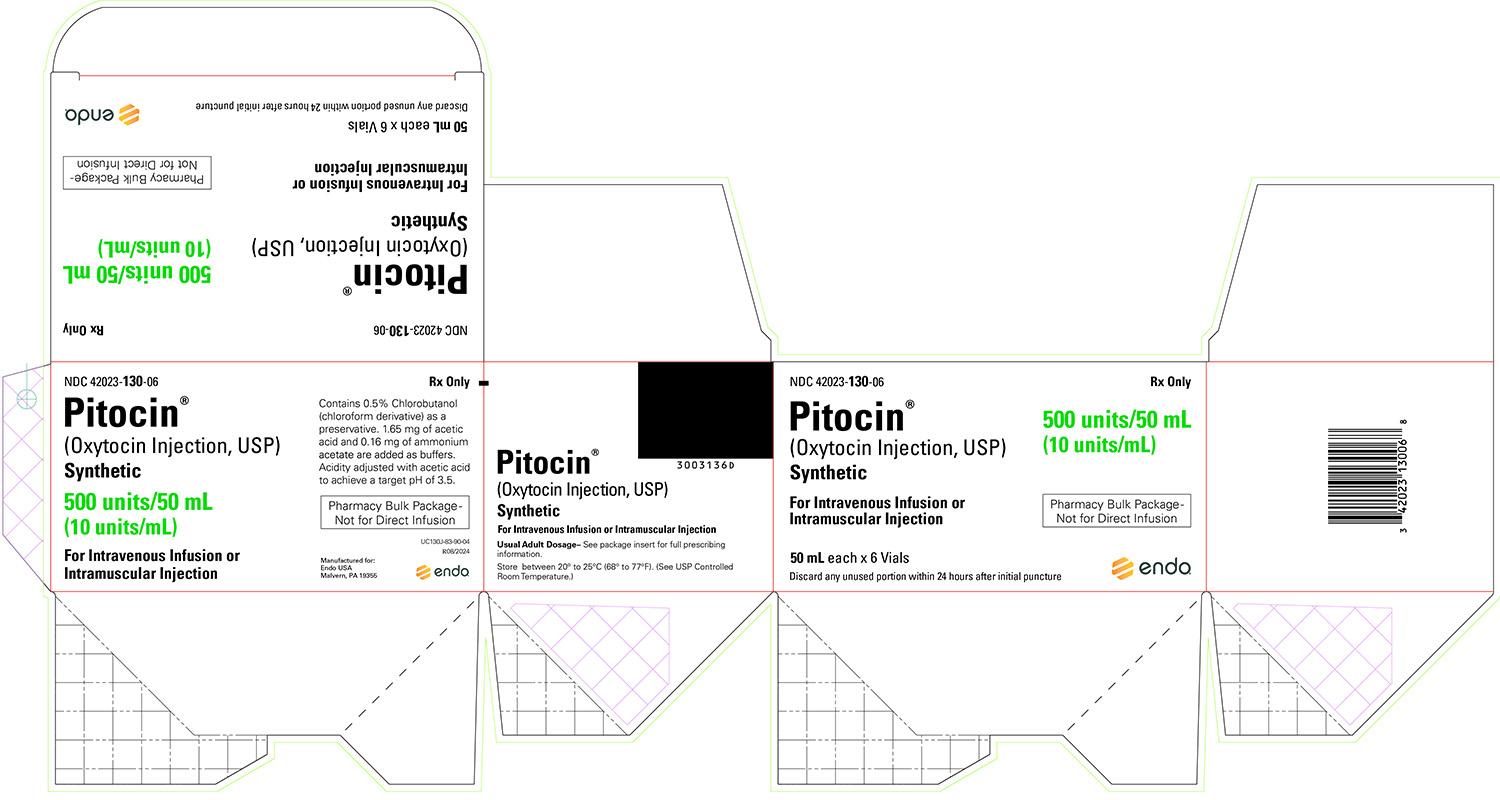 DRUG LABEL: Pitocin
NDC: 42023-130 | Form: INJECTION
Manufacturer: Par Health USA, LLC
Category: prescription | Type: HUMAN PRESCRIPTION DRUG LABEL
Date: 20240813

ACTIVE INGREDIENTS: OXYTOCIN 10 [iU]/1 mL
INACTIVE INGREDIENTS: CHLOROBUTANOL; ACETIC ACID

Pitocin®
(Oxytocin Injection, USP) Synthetic

Pharmacy Bulk Package – Not for Direct Infusion

DESCRIPTION

Pitocin (oxytocin injection, USP) is a sterile, clear, colorless aqueous solution of synthetic oxytocin, for intravenous infusion or intramuscular injection. Pitocin is a nonapeptide found in pituitary extracts from mammals. It is standardized to contain 10 units of oxytocic hormone/mL and contains 0.5% Chlorobutanol, a chloroform derivative as a preservative, 1.65 mg acetic acid and 0.16 mg ammonium acetate as buffers, and with the pH adjusted with acetic acid to achieve a targeted pH of 3.5. Pitocin may contain up to 16% of total impurities. The hormone is prepared synthetically to avoid possible contamination with vasopressin (ADH) and other small polypeptides with biologic activity. Pitocin has the empirical formula C43H66N12O12S2 (molecular weight 1007.19). The structural formula is as follows:

CLINICAL PHARMACOLOGY

Uterine motility depends on the formation of the contractile protein actomyosin under the influence of the Ca^2+- dependent phosphorylating enzyme myosin light-chain kinase. Oxytocin promotes contractions by increasing the intracellular Ca^2+. Oxytocin has specific receptors in the myometrium and the receptor concentration increases greatly during pregnancy, reaching a maximum in early labor at term. The response to a given dose of oxytocin is very individualized and depends on the sensitivity of the uterus, which is determined by the oxytocin receptor concentration. However, the physician should be aware of the fact that oxytocin even in its pure form has inherent pressor and antidiuretic properties which may become manifest when large doses are administered. These properties are thought to be due to the fact that oxytocin and vasopressin differ in regard to only two of the eight amino acids (see PRECAUTIONS section).

Oxytocin is distributed throughout the extracellular fluid. Small amounts of the drug probably reach the fetal circulation. Oxytocin has a plasma half-life of about 1 to 6 minutes which is decreased in late pregnancy and during lactation. Following intravenous administration of oxytocin, uterine response occurs almost immediately and subsides within 1 hour. Following intramuscular injection of the drug, uterine response occurs within 3 to 5 minutes and persists for 2 to 3 hours. Its rapid removal from plasma is accomplished largely by the kidney and the liver. Only small amounts are excreted in urine unchanged.

INDICATIONS AND USAGE

IMPORTANT NOTICE

Elective induction of labor is defined as the initiation of labor in a pregnant individual who has no medical indications for induction. Since the available data are inadequate to evaluate the benefits-to-risks considerations, Pitocin is not indicated for elective induction of labor.

Antepartum: Pitocin is indicated for the initiation or improvement of uterine contractions, where this is desirable and considered suitable for reasons of fetal or maternal concern, in order to achieve vaginal delivery. It is indicated for (1) induction of labor in patients with a medical indication for the initiation of labor, such as Rh problems, maternal diabetes, preeclampsia at or near term, when delivery is in the best interests of mother and fetus or when membranes are prematurely ruptured and delivery is indicated; (2) stimulation or reinforcement of labor, as in selected cases of uterine inertia; (3) as adjunctive therapy in the management of incomplete or inevitable abortion. In the first trimester, curettage is generally considered primary therapy. In second trimester abortion, oxytocin infusion will often be successful in emptying the uterus. Other means of therapy, however, may be required in such cases.

Postpartum: Pitocin is indicated to produce uterine contractions during the third stage of labor and to control postpartum bleeding or hemorrhage.

CONTRAINDICATIONS

Antepartum use of Pitocin is contraindicated in any of the following circumstances:

1. Where there is significant cephalopelvic disproportion;
2. In unfavorable fetal positions or presentations, such as transverse lies, which are undeliverable without conversion prior to delivery;
3. In obstetrical emergencies where the benefit-to-risk ratio for either the fetus or the mother favors surgical intervention;
4. In fetal distress where delivery is not imminent;
5. Where adequate uterine activity fails to achieve satisfactory progress;
6. Where the uterus is already hyperactive or hypertonic;
7. In cases where vaginal delivery is contraindicated, such as invasive cervical carcinoma, active herpes genitalis, total placenta previa, vasa previa, and cord presentation or prolapse of the cord;
8. In patients with hypersensitivity to the drug.

WARNINGS

Pitocin, when given for induction of labor or augmentation of uterine activity, should be administered only by the intravenous route and with adequate medical supervision in a hospital.

PRECAUTIONS

General

1. All patients receiving intravenous oxytocin must be under continuous observation by trained personnel who have a thorough knowledge of the drug and are qualified to identify complications. A physician qualified to manage any complications should be immediately available. Electronic fetal monitoring provides the best means for early detection of overdosage (see OVERDOSAGE section). However, it must be borne in mind that only intrauterine pressure recording can accurately measure the intrauterine pressure during contractions. A fetal scalp electrode provides a more dependable recording of the fetal heart rate than any external monitoring system.
2. When properly administered, oxytocin should stimulate uterine contractions comparable to those seen in normal labor. Overstimulation of the uterus by improper administration can be hazardous to both mother and fetus. Even with proper administration and adequate supervision, hypertonic contractions can occur in patients whose uteri are hypersensitive to oxytocin. This fact must be considered by the physician in exercising his judgment regarding patient selection.
3. Except in unusual circumstances, oxytocin should not be administered in the following conditions: fetal distress, hydramnios, partial placenta previa, prematurity, borderline cephalopelvic disproportion, and any condition in which there is a predisposition for uterine rupture, such as previous major surgery on the cervix or uterus including cesarean section, overdistention of the uterus, grand multiparity, or past history of uterine sepsis or of traumatic delivery. Because of the variability of the combinations of factors which may be present in the conditions listed above, the definition of "unusual circumstances" must be left to the judgment of the physician. The decision can be made only by carefully weighing the potential benefits which oxytocin can provide in a given case against rare but definite potential for the drug to produce hypertonicity or tetanic spasm.
4. Maternal deaths due to hypertensive episodes, subarachnoid hemorrhage, rupture of the uterus, and fetal deaths due to various causes have been reported associated with the use of parenteral oxytocic drugs for induction of labor or for augmentation in the first and second stages of labor.
5. Oxytocin has been shown to have an intrinsic antidiuretic effect, acting to increase water reabsorption from the glomerular filtrate. Consideration should, therefore, be given to the possibility of water intoxication, particularly when oxytocin is administered continuously by infusion and the patient is receiving fluids by mouth.
6. When oxytocin is used for induction or reinforcement of already existent labor, patients should be carefully selected. Pelvic adequacy must be considered and maternal and fetal conditions evaluated before use of the drug.

Drug Interactions

Severe hypertension has been reported when oxytocin was given three to four hours following prophylactic administration of a vasoconstrictor in conjunction with caudal block anesthesia. Cyclopropane anesthesia may modify oxytocin's cardiovascular effects, so as to produce unexpected results such as hypotension. Maternal sinus bradycardia with abnormal atrioventricular rhythms has also been noted when oxytocin was used concomitantly with cyclopropane anesthesia.

Carcinogenesis, Mutagenesis, Impairment of Fertility

There are no animal or human studies on the carcinogenicity and mutagenicity of this drug, nor is there any information on its effect on fertility.

Pregnancy

Teratogenic Effects

Animal reproduction studies have not been conducted with oxytocin. There are no known indications for use in the first trimester of pregnancy other than in relation to spontaneous or induced abortion. Based on the wide experience with this drug and its chemical structure and pharmacological properties, it would not be expected to present a risk of fetal abnormalities when used as indicated.

Nonteratogenic Effects

See ADVERSE REACTIONS in the fetus or neonate.

Labor and Delivery

See INDICATIONS AND USAGE section.

ADVERSE REACTIONS

The following adverse reactions have been reported in the mother:

Anaphylactic reaction | Premature ventricular contractions
Postpartum hemorrhage | Pelvic hematoma
Cardiac arrhythmia | Subarachnoid hemorrhage
Fatal afibrinogenemia | Hypertensive episodes
Nausea | Rupture of the uterus
Vomiting

Excessive dosage or hypersensitivity to the drug may result in uterine hypertonicity, spasm, tetanic contraction, or rupture of the uterus.

The possibility of increased blood loss and afibrinogenemia should be kept in mind when administering the drug.

Severe water intoxication with convulsions and coma has occurred, associated with a slow oxytocin infusion over a 24-hour period. Maternal death due to oxytocin-induced water intoxication has been reported.

The following adverse reactions have been reported in the fetus or neonate:

Due to induced uterine motility: | Due to use of oxytocin in the mother:
Bradycardia | Low Apgar scores at five minutes
Premature ventricular contractions and other arrhythmias | Neonatal jaundice
Permanent CNS or brain damage | Neonatal retinal hemorrhage
Fetal death
Neonatal seizures have been reported with the use of Pitocin.

For medical advice about adverse reactions contact your medical professional. To report SUSPECTED ADVERSE REACTIONS, contact Endo at 1-800-828-9393 or FDA at 1-800-FDA-1088 (1-800-332-1088) or www.fda.gov/medwatch.

OVERDOSAGE

Overdosage with oxytocin depends essentially on uterine hyperactivity whether or not due to hypersensitivity to this agent. Hyperstimulation with strong (hypertonic) or prolonged (tetanic) contractions, or a resting tone of 15 to 20 mmHg or more between contractions can lead to tumultuous labor, uterine rupture, cervical and vaginal lacerations, postpartum hemorrhage, uteroplacental hypoperfusion, and variable deceleration of fetal heart, fetal hypoxia, hypercapnia, perinatal hepatic necrosis or death. Water intoxication with convulsions, which is caused by the inherent antidiuretic effect of oxytocin, is a serious complication that may occur if large doses (40 to 50 milliunits/minute) are infused for long periods. Management consists of immediate discontinuation of oxytocin and symptomatic and supportive therapy.

DOSAGE AND ADMINISTRATION

Parenteral drug products should be inspected visually for particulate matter and discoloration prior to administration whenever solution and container permit.

The dosage of oxytocin is determined by the uterine response and must therefore be individualized and initiated at a very low level. The following dosage information is based upon various regimens and indications in general use.

A. Induction or Stimulation of Labor

Intravenous infusion (drip method) is the only acceptable method of parenteral administration of Pitocin for the induction or stimulation of labor. Accurate control of the rate of infusion is essential and is best accomplished by an infusion pump. It is convenient to piggyback the Pitocin infusion on a physiologic electrolyte solution, permitting the Pitocin infusion to be stopped abruptly without interrupting the electrolyte infusion. This is done in the following way.

1. Preparation

a. The standard solution for infusion of Pitocin is prepared by adding 1 mL (containing 10 units of oxytocin) to 1000 mL of 0.9% aqueous sodium chloride or Ringer’s lactate. The combined solution containing 10 milliunits (mU) of oxytocin/mL is rotated in the infusion bottle for thorough mixing.

b. Establish the infusion with a separate bottle of physiologic electrolyte solution not containing Pitocin.

c. Attach (piggyback) the Pitocin-containing bottle with the infusion pump to the infusion line as close to the infusion site as possible.

2. Administration

The initial dose should be 0.5–1 mU/min (equal to 3–6 mL of the dilute oxytocin solution per hour). At 30–60 minute intervals the dose should be gradually increased in increments of 1–2 mU/min until the desired contraction pattern has been established. Once the desired frequency of contractions has been reached and labor has progressed to 5–6 cm dilation, the dose may be reduced by similar increments.
Studies of the concentrations of oxytocin in the maternal plasma during Pitocin infusion have shown that infusion rates up to 6 mU/min give the same oxytocin levels that are found in spontaneous labor. At term, higher infusion rates should be given with great care, and rates exceeding 9–10 mU/min are rarely required. Before term, when the sensitivity of the uterus is lower because of a lower concentration of oxytocin receptors, a higher infusion rate may be required.

3. Monitoring

a. Electronically monitor the uterine activity and the fetal heart rate throughout the infusion of Pitocin. Attention should be given to tonus, amplitude and frequency of contractions, and to the fetal heart rate in relation to uterine contractions. If uterine contractions become too powerful, the infusion can be abruptly stopped, and oxytocic stimulation of the uterine musculature will soon wane (see PRECAUTIONS section).

b. Discontinue the infusion of Pitocin immediately in the event of uterine hyperactivity and/or fetal distress. Administer oxygen to the mother, who preferably should be put in a lateral position. The condition of mother and fetus should immediately be evaluated by the responsible physician and appropriate steps taken.

B. Control of Postpartum Uterine Bleeding

1. Intravenous infusion (drip method). If the patient has an intravenous infusion running, 10 to 40 units of oxytocin may be added to the bottle, depending on the amount of electrolyte or dextrose solution remaining (maximum 40 units to 1000 mL). Adjust the infusion rate to sustain uterine contraction and control uterine atony.
2. Intramuscular administration. 1 mL (10 units) of Pitocin can be given after the delivery of the placenta.

C. Treatment of Incomplete, Inevitable, or Elective Abortion

Intravenous infusion of 10 units of Pitocin added to 500 mL of a physiologic saline solution or 5% dextrose-in-water solution may help the uterus contract after a suction or sharp curettage for an incomplete, inevitable, or elective abortion.

Subsequent to intra-amniotic injection of hypertonic saline, prostaglandins, urea, etc., for midtrimester elective abortion, the injection-to-abortion time may be shortened by infusion of Pitocin at the rate of 10 to 20 milliunits (20 to 40 drops) per minute. The total dose should not exceed 30 units in a 12-hour period due to the risk of water intoxication.

Directions for Dispensing

Pharmacy Bulk Package – Not for Direct Infusion: The pharmacy bulk package is for use in a pharmacy admixture service only in a suitable work area, such as a laminar flow hood. The closure should be penetrated only once utilizing an appropriate sterile transfer device, which allows measured distribution of the contents. The transfer device should be inserted into the Pharmacy Bulk Package using aseptic technique.

Contents should be used as soon as possible following initial closure puncture. Discard any unused portion within 24 hours of first entry. Following closure puncture, container should be maintained under labeled storage conditions between 20° to 25°C (68° to 77°F) under a laminar flow hood until contents are dispensed.

HOW SUPPLIED

Pitocin (Oxytocin Injection, USP) Synthetic is available as follows:

NDC 42023-130-06 Packages of six 50 mL Pharmacy Bulk Packages, each containing 10 units of oxytocin per mL (total = 500 units of oxytocin per vial).

STORAGE

Store between 20° to 25°C (68° to 77°F). (See USP Controlled Room Temperature.)

REFERENCES

1. Seitchik J, Castillo M: Oxytocin augmentation of dysfunctional labor. I. Clinical data. Am J Obstet Gynecol 1982; 144:899–905.
2. Seitchik J, Castillo M: Oxytocin augmentation of dysfunctional labor. II. Multiparous patients. Am J Obstet Gynecol 1983; 145:777–780.
3. Fuchs A, Goeschen K, Husslein P, et al: Oxytocin and the initiation of human parturition. III. Plasma concentrations of oxytocin and 13, 14-dihydro-15-keto-prostaglandin F2a in spontaneous and oxytocin-induced labor at term. Am J Obstet Gynecol 1983; 145:497–502.
4. Seitchik J, Amico J, et al: Oxytocin augmentation of dysfunctional labor. IV. Oxytocin pharmacokinetics. Am J Obstet Gynecol 1984; 150:225–228.
5. American College of Obstetricians and Gynecologists: ACOG Technical Bulletin Number 110—November 1987: Induction and augmentation of labor.

Rx only.

Manufactured for:

Endo USA

Malvern, PA 19355

© 2024 Endo, Inc. or one of its affiliates.

Revised: August 2024